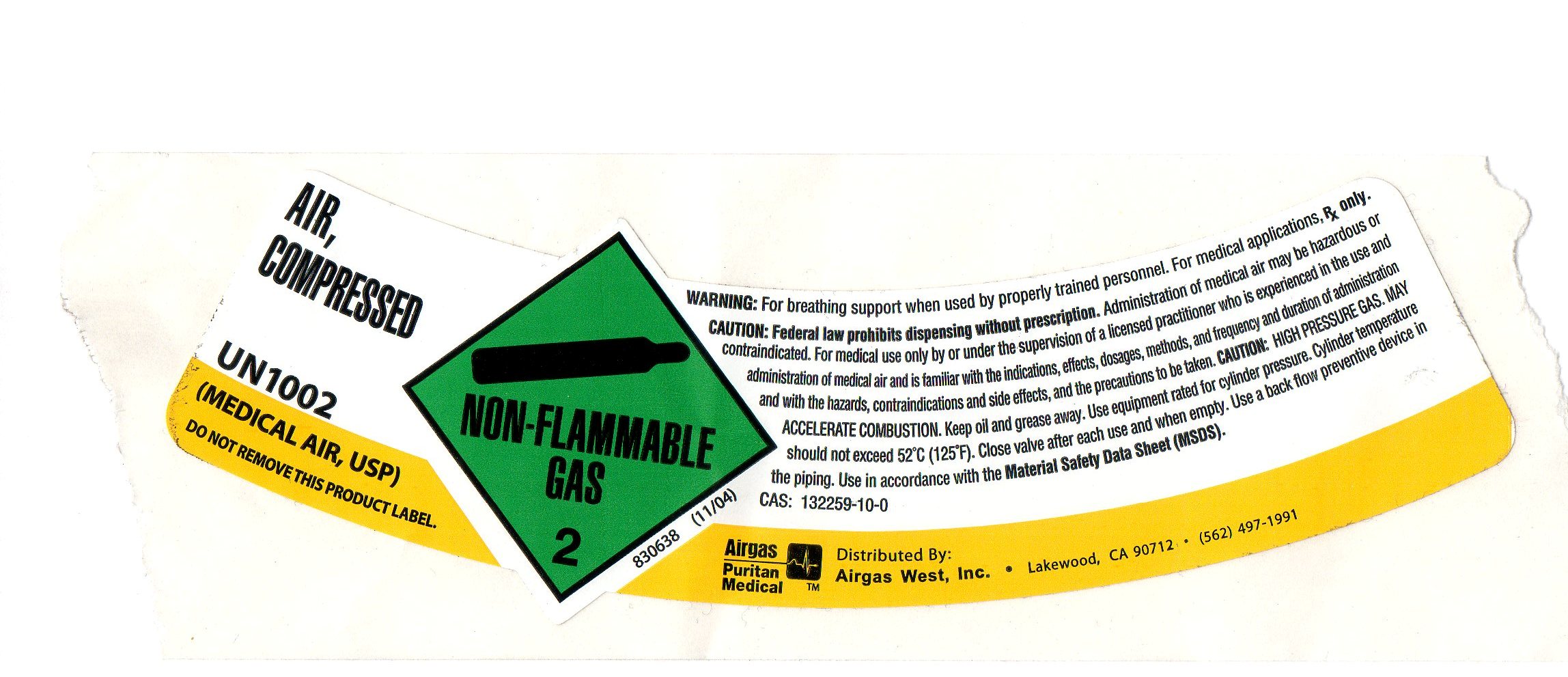 DRUG LABEL: Air
NDC: 10678-005 | Form: GAS
Manufacturer: Airgas-West, Inc.
Category: prescription | Type: HUMAN PRESCRIPTION DRUG LABEL
Date: 20100816

ACTIVE INGREDIENTS: Air 1000 mL/1 L

air

PACKAGE LABEL

AIR, COMPRESSED
UN1002 (MEDICAL AIR, USP) DO NOT REMOVE THIS PRODUCT LABEL.
WARNING: For breathing support when used by properly trained personnel. For medical applications, Rx only. CAUTION: federal law prohibits xxx without xxx. Administration of medical air may be hazardous or contraindicated. For medical use only by or under the supervision of a xxx practitioner who is experienced in the use and administration of medical air and is familiar with the xxx, effects, dosage, xxx and frequency and duration of administration and with hazards, contraindications and side effects, and the precautions to be taken. CAUTION: HIGH PRESSURE GAS. MAY ACCELERATE COMBUSTION. Keep oil and grease away. Use equipment rated for cylinder pressure. Cylinder temperature should not exceed 52 degrees C (125 degrees F). close valve after each use and when empty. Use a back flow preventative device in the piping. Use in accordance with the Material Safety Data Sheet (MSDS). CAS: 132259-10-0
Airgas Puritan Medical
Distributed By: Airgas West, Inc.
Lakewood, CA 90712
502-497-1991